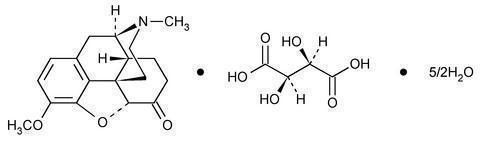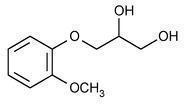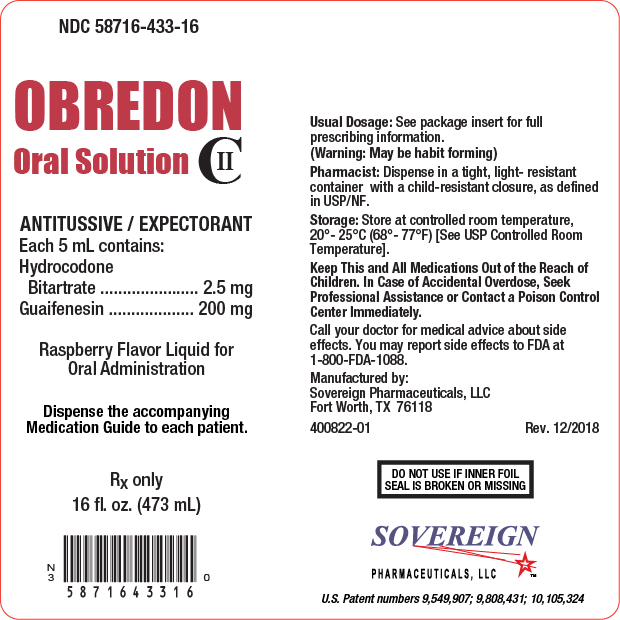 DRUG LABEL: OBREDON
NDC: 58716-433 | Form: SOLUTION
Manufacturer: Sovereign Pharmaceuticals, LLC
Category: prescription | Type: HUMAN PRESCRIPTION DRUG LABEL
Date: 20241014
DEA Schedule: CII

ACTIVE INGREDIENTS: HYDROCODONE BITARTRATE 2.5 mg/5 mL; GUAIFENESIN 200 mg/5 mL
INACTIVE INGREDIENTS: CITRIC ACID MONOHYDRATE; GLYCERIN; METHYLPARABEN; POTASSIUM CITRATE; POTASSIUM SORBATE; PROPYLENE GLYCOL; PROPYLPARABEN; WATER; SACCHARIN SODIUM

HIGHLIGHTS OF PRESCRIBING INFORMATION

These highlights do not include all the information needed to use OBREDON®safely and effectively. See full prescribing information for OBREDON.
OBREDON (hydrocodone bitartrate and guaifenesin) oral solution CII
Initial U.S. Approval: 2014

BOXED WARNING

WARNING: ADDICTION, ABUSE, AND MISUSE; LIFETHREATENING RESPIRATORY DEPRESSION; ACCIDENTAL INGESTION; MEDICATION ERRORS; CYTOCHROME P450 3A4 INTERACTION; CONCOMITANT USE WITH BENZODIAZEPINES OR OTHER CNS DEPRESSANTS; INTERACTION WITH ALCOHOL; NEONATAL OPIOID WITHDRAWAL SYNDROME

See full prescribing information for complete boxed warning.

- OBREDON exposes users to risks of addiction, abuse, and misuse, which can lead to overdose and death. Assess patient’s risk before prescribing and monitor closely for these behaviors and conditions. (5.1)
- Serious, life-threatening, or fatal respiratory depression may occur. Monitor closely, especially upon initiation or when used in patients at higher risk. (5.2)
- Accidental ingestion of OBREDON, especially by children, can result in a fatal overdose of hydrocodone. (5.2)
- Ensure accuracy when prescribing, dispensing, and administering OBREDON. Dosing errors can result in accidental overdose and death. (2.1, 5.5)
- Concomitant use with CYP3A4 inhibitors (or discontinuation of CYP3A4 inducers) can result in a fatal overdose of hydrocodone. Avoid the use of OBREDON in patients taking CYP3A4 inhibitors or inducers. (5.7, 7.2, 7.3)
- Concomitant use of opioids with benzodiazepines or other central nervous system (CNS) depressants, including alcohol, may result in profound sedation, respiratory depression, coma, and death. Avoid the use of OBREDON in patients taking benzodiazepines, other CNS depressants, or alcohol. (5.8, 7.4)
- Instruct patients not to consume alcohol or any products containing alcohol while taking OBREDON because co-ingestion can result in fatal plasma hydrocodone levels. (5.8, 7.1)
- OBREDON is not recommended for use in pregnant women. Prolonged use of OBREDON during pregnancy can result in neonatal opioid withdrawal syndrome, which may be lifethreatening if not recognized and treated. If OBREDON is used for a prolonged period in a pregnant woman, advise the patient of the risk of neonatal opioid withdrawal syndrome and ensure that appropriate treatment will be available. (5.13, 8.1)

1 INDICATIONS AND USAGE

OBREDON is a combination of hydrocodone, an opioid agonist; and guaifenesin, an expectorant, indicated for the symptomatic relief of cough and to loosen mucus associated with the common cold in patients 18 years of age and older. (1)

Important Limitations of Use: (1)

- Not indicated for pediatric patients under 18 years of age.
- Because of the risks of addiction, abuse, and misuse with opioids, even at recommended doses, reserve OBREDON for use in adult patients for
  whom the benefits of cough suppression are expected to outweigh the risks, and in whom an adequate assessment of the etiology of the cough has been made.

2 DOSAGE AND ADMINISTRATION

Adults 18 years of age and older:10 mL every 4 to 6 hours as needed, not to exceed 6 doses (60 mL) in 24 hours. (2.2)

- Measure OBREDON with an accurate milliliter measuring device. (2.1, 5.5)
- Do not increase the dose or dosing frequency. (2.1)

3 DOSAGE FORMS AND STRENGTHS

Oral solution: Each 5 mL contains hydrocodone bitartrate 2.5 mg; and guaifenesin 200 mg.(3)

4 CONTRAINDICATIONS

- Children younger than 6 years of age. (4)
- Significant respiratory depression. (4)
- Acute or severe bronchial asthma in an unmonitored setting or in absence of resuscitative equipment. (4)
- Known or suspected gastrointestinal obstruction, including paralytic ileus. (4)
- Hypersensitivity to hydrocodone, guaifenesin, or any of the inactive ingredients in OBREDON. (4)

5 WARNINGS AND PRECAUTIONS

See Boxed WARNINGS

- Life-threatening respiratory depression in patients with chronic pulmonary disease or in elderly, cachectic, or debilitated patients:Monitor closely, particularly during initiation of therapy. (5.4)
- Activities requiring mental alertness:Avoid engaging in hazardous tasks requiring mental alertness such as driving or operating machinery. (5.6)
- Risks of use in patients with head injury, impaired consciousness, increased intracranial pressure, or brain tumors:Avoid use. May increase intracranial pressure and obscure the clinical course of head injuries. (5.10)
- Seizures in patients with seizure disorders:Monitor during therapy. (5.11)
- Severe hypotension:Monitor during initiation of therapy. Avoid use in patients with circulatory shock. (5.12)
- Adrenal insufficiency:If diagnosed, treat with physiologic replacement of corticosteroids, and wean patient off of the opioid. (5.14)

6 ADVERSE REACTIONS

Common adverse reactions include: Sedation (somnolence, mental clouding, lethargy), impaired mental and physical performance, lightheadedness, dizziness, headache, dry mouth, nausea, vomiting, and constipation (6)

To report SUSPECTED ADVERSE REACTIONS, contact Sovereign Pharmaceuticals, LLC at 1-855-461-5102 or FDA at 1-800-FDA-1088 or www.fda.gov/medwatch.

7 DRUG INTERACTIONS

- Serotonergic Drugs:Concomitant use may result in serotonin syndrome. Discontinue if serotonin syndrome is suspected. (7.5)
- Monoamine Oxidase Inhibitors (MAOIs):Can potentiate the effects of hydrocodone. Avoid concomitant use in patients receiving MAOIs or within 14 days of stopping an MAOI. (7.6)
- Muscle Relaxants:Avoid concomitant use. (7.7)
- Diuretics:Hydrocodone may reduce the efficacy of diuretics. Monitor for reduced effect. (7.8)
- Anticholinergic drugs:Concomitant use may cause paralytic ileus. (5.9, 7.9)

8 USE IN SPECIFIC POPULATIONS

- Pregnancy:Avoid use in pregnant women. May cause fetal harm. (8.1)
- Lactation:Breastfeeding not recommended. (8.2)
- Renal Impairment:Use with caution in patients with severe renal impairment. (8.6)
- Hepatic Impairment:Use with caution in patients with severe hepatic impairment. (8.7)

FULL PRESCRIBING INFORMATION

BOXED WARNING

WARNING: ADDICTION, ABUSE, AND MISUSE; LIFE-THREATENING RESPIRATORY DEPRESSION; ACCIDENTAL INGESTION; MEDICATION ERRORS; CYTOCHROME P450 3A4 INTERACTION; CONCOMITANT USE WITH BENZODIAZEPINES OR OTHER CNS
DEPRESSANTS; INTERACTION WITH ALCOHOL; NEONATAL OPIOID WITHDRAWAL SYNDROME

Addiction, Abuse, and Misuse
OBREDON exposes patients and other users to the risks of opioid addiction, abuse, and misuse, which can lead to overdose and death. Reserve OBREDON for use in adult patients for whom the benefits of cough suppression are expected to outweigh the risks, and in whom an adequate assessment of the etiology of the cough has been made. Assess each patient’s risk prior to
prescribing OBREDON, prescribe OBREDON for the shortest duration that is consistent with individual patient treatment goals, monitor all patients regularly for the development of addition or abuse, and refill only after reevaluation of the need for continued treatment. [ see Warnings and Precautions (5.1) ]

Life-Threatening Respiratory Depression
Serious, life-threatening, or fatal respiratory depression may occur with use of OBREDON. Monitor for respiratory depression, especially during initiation of OBREDON therapy or when used in patients at higher risk [ see Warnings and Precautions (5.2) ].

Accidental Ingestion
Accidental ingestion of even one dose of OBREDON, especially by children, can result in a fatal overdose of hydrocodone [ see Warnings and Precautions (5.2) ].

Risk of Medication Errors
Ensure accuracy when prescribing, dispensing, and administering OBREDON. Dosing errors can result in accidental overdose and death. Always use an accurate milliliter measuring device when measuring and administering OBREDON [ see Dosage and Administration (2.1), Warnings and Precautions (5.5) ].

Cytochrome P450 3A4 Interaction The concomitant use of OBREDON with all cytochrome P450 3A4 inhibitors may result in an increase in hydrocodone plasma concentrations, which could increase or prolong adverse drug effects and may cause potentially fatal respiratory depression. In addition, discontinuation of a concomitantly used cytochrome P450 3A4 inducer may result in an increase in hydrocodone plasma concentration. Avoid the use of OBREDON in patients taking a CYP3A4 inhibitor or inducer [ see Warnings and Precautions (5.7), Drug Interactions (7.2, 7.3) ].

Risks from Concomitant Use with Benzodiazepines or Other CNS Depressants Concomitant use of opioids with benzodiazepines or other central nervous system (CNS) depressants, including alcohol, may result in profound sedation, respiratory depression, coma, and death. Avoid the use of OBREDON in patients taking benzodiazepines, other CNS depressants, or alcohol. [see Warning and Precautions (5.8), Drug Interactions (7.4)].

Interaction with Alcohol
Instruct patients not to consume alcoholic beverages or use prescription or non-prescription products that contain alcohol while taking OBREDON. The co-ingestion of alcohol with OBREDON may result in increased plasma levels and a potentially fatal overdose of hydrocodone [ see Warnings and Precautions (5.8), Drug Interactions (7.1) ].

Neonatal Opioid Withdrawal Syndrome
OBREDON is not recommended for use in pregnant women [ see Use in Specific Populations (8.1) ]. Prolonged use of OBREDON during pregnancy can result in neonatal opioid withdrawal syndrome, which may be life-threatening if not recognized and treated, and requires management according to protocols developed by neonatology experts. If OBREDON is used for a prolonged period in a pregnant woman, advise the patient of the risk of neonatal opioid withdrawal syndrome and ensure that appropriate treatment will be available [ see Warnings and Precautions (5.13) ]

1 INDICATIONS AND USAGE

OBREDON is indicated for the symptomatic relief of cough and to loosen mucus associated with the common cold in patients 18 years of age and older.

Important Limitations of Use

- Not indicated for pediatric patients under 18 years of age [ see Use in Specific Populations (8.4) ].
- Contraindicated in pediatric patients less than 6 years of age [ see Contraindications (4) ]
- Because of the risks of addiction, abuse, and misuse with opioids, even at recommended doses, reserve OBREDON for use in adult patients for whom the benefits of cough suppression are expected to outweigh the risks, and in whom an adequate assessment of the etiology of the cough has been made.

2 DOSAGE AND ADMINISTRATION

2.1 Important Dosage and Administration Instructions

Administer OBREDON by the oral route only

Always use an accurate milliliter measuring device when administering OBREDON to ensure that the dose is measured and administered accurately. A household teaspoon is not an accurate measuring device and could lead to overdosage [ see Warnings and Precautions (5.5) ]. For prescriptions where a measuring device is not provided, a pharmacist can provide an appropriate measuring device and can provide instructions for measuring the correct dose. Do not overfill. Rinse the measuring device with water after each use.

Advise patients not to increase the dose or dosing frequency of OBREDON because serious adverse events such as respiratory depression may occur with overdosage [ see Warnings and Precautions (5.2), Overdosage (10) ]. The dosage of OBREDON should not be increased if cough fails to respond; an unresponsive cough should be reevaluated for possible underlying pathology [ see Dosage and Administration (2.3), Warnings and Precautions (5.4) ].

2.2 Recommended Dosage

Adults and adolescents 18 years of age and older:10 mL every 4 to 6 hours, not to exceed 6 doses (60 mL) in 24 hours.

2.3 Monitoring, Maintenance, and Discontinuation of Therapy

Prescribe OBREDON for the shortest duration that is consistent with individual patient treatment goals [ see Warnings and Precautions (5.1) ].

Monitor patients closely for respiratory depression, especially within the first 24-72 hours of initiating therapy [ see Warnings and Precautions (5.2) ].

Reevaluate patients with unresponsive cough in 5 days or sooner for possible underlying pathology, such as foreign body or lower respiratory tract disease [ see Warnings and Precautions (5.4) ]. If a patient requires a refill, reevaluate the cause of the cough and assess the need for continued treatment with OBREDON, the relative incidence of adverse reactions, and the development of addiction, abuse, or misuse [ see Warnings and Precautions (5.1) ].

Do not abruptly discontinue OBREDON in a physically-dependent patient [ see Drug Abuse and Dependence (9.3) ]. When a patient who has been taking OBREDON regularly and may be physically dependent no longer requires therapy with OBREDON, taper the dose gradually, by 25% to 50% every 2 to 4 days, while monitoring carefully for signs and symptoms of withdrawal. If the patient develops these signs or symptoms, raise the dose to the previous level and taper more slowly, either by increasing the interval between decreases, decreasing the amount of change in dose, or both.

3 DOSAGE FORMS AND STRENGTHS

Oral Solution: Each 5 mL contains hydrocodone bitartrate, USP, 2.5 mg; and guaifenesin, USP, 200 mg [ see Description (11) ].

4 CONTRAINDICATIONS

OBREDON is contraindicated for:

- All children younger than 6 years of age [ see Warnings and Precautions (5.2, 5.3), Use in Specific Populations (8.4) ].

OBREDON is also contraindicated in patients with:

- Significant respiratory depression [ see Warnings and Precautions (5.2) ].
- Acute or severe bronchial asthma in an unmonitored setting or in the absence of resuscitative equipment [ see Warnings and Precautions (5.4) ].
- Known or suspected gastrointestinal obstruction, including paralytic ileus [ see Warnings and Precautions (5.9) ].
- Hypersensitivity to hydrocodone, guaifenesin, or any of the inactive ingredients in OBREDON [ see Adverse Reactions (6) ].

5 WARNINGS AND PRECAUTIONS

5.1 Addiction, Abuse, and Misuse

OBREDON contains hydrocodone, a Schedule II controlled substance. As an opioid, OBREDON exposes users to the risks of addiction, abuse, and misuse [ see Drug Abuse and Dependence (9) ], which can lead to overdose and death [ see Overdosage (10) ]. Reserve OBREDON for use in adult patients for whom the benefits of cough suppression are expected to outweigh the risks, and in whom an adequate assessment of the etiology of the cough has been made. Assess each patient’s risk prior to prescribing OBREDON, prescribe OBREDON for the shortest duration that is consistent with individual patient treatment goals, monitor all patients regularly for the development of addiction or abuse, and refill only after reevaluation of the need for continued treatment.

Although the risk of addiction in any individual is unknown, it can occur in patients appropriately prescribed OBREDON. Addiction can occur at recommended dosages and if the drug is misused or abused. Risks are increased in patients with a personal or family history of substance abuse (including drug or alcohol abuse or addiction) or mental illness (e.g., major depression).

Opioids are sought by drug abusers and people with addiction disorders and are subject to criminal diversion. Consider these risks when prescribing or dispensing OBREDON. Strategies to reduce these risks include prescribing the drug in the smallest appropriate quantity and advising the patient on the proper disposal of unused drug [ see Patient Counseling Information (17) ]. Contact local state professional licensing board or state controlled substances authority for information on how to prevent and detect abuse or diversion of this product.

5.2 Life-Threatening Respiratory Depression

Serious, life-threatening, or fatal respiratory depression has been reported with the use of opioids, including hydrocodone, one of the active ingredients in OBREDON. Hydrocodone produces dose-related respiratory depression by directly acting on the brain stem respiratory center that controls respiratory rhythm and may produce irregular and periodic breathing. Respiratory depression, if not immediately recognized and treated,
may lead to respiratory arrest and death. Management of respiratory depression includes discontinuation of OBREDON, close observation, supportive measures, and use of opioid antagonists (e.g. naloxone), depending on the patient’s clinical status [ see Overdosage (10) ]. Carbon dioxide (CO2) retention from opioid-induced respiratory depression can exacerbate the sedating effects of opioids.

While serious, life-threatening, or fatal respiratory depression can occur at any time during the use of OBREDON, the risk is greatest during the initiation of therapy, when OBREDON is used concomitantly with other drugs that may cause respiratory depression [ see Warnings and Precautions (5.8) ], in patients with chronic pulmonary disease or decreased respiratory reserve, and in patients with altered pharmacokinetics or altered clearance (e.g. elderly, cachectic, or debilitated patients) [ see Warnings and Precautions (5.4) ].

To reduce the risk of respiratory depression, proper dosing of OBREDON is essential [ see Dosage and Administration (2.1), Warnings and Precautions (5.5) ]. Monitor patients closely, especially within the first 24- 72 hours of initiating therapy or when used in patients at higher risk.

Overdose of hydrocodone in adults has been associated with fatal respiratory depression, and the use of hydrocodone in children younger than 6 years of age has been associated with fatal respiratory depression when used as recommended. Accidental ingestion of even one dose of OBREDON, especially by children, can result in respiratory depression and death.

5.3 Risks with Use in Pediatric Populations

Children are particularly sensitive to the respiratory depressant effects of hydrocodone [ see Warnings and Precautions (5.2) ]. Because of the risk of life-threatening respiratory depression and death, OBREDON is contraindicated in children less than 6 years of age [ see Contraindications (4) ].

Use of OBREDON in children also exposes them to the risks of addiction, abuse, and misuse [ see Drug Abuse and Dependence (9) ], which can lead to overdose and death [ see Warnings and Precautions (5.1), Overdosage (10) ]. Because the benefits of symptomatic treatment of cough associated with allergies or the common cold do not outweigh the risks of use of hydrocodone in pediatric patients, OBREDON is not indicated for use in patients younger than 18 years of age [ see Indications (1), Use in Specific Populations (8.4) ].

5.4 Risks with Use in Other At-Risk Populations

Unresponsive CoughThe dosage of OBREDON should not be increased if cough fails to respond; an unresponsive cough should be reevaluated in 5 days or sooner for possible underlying pathology, such as foreign body or lower respiratory tract disease [ see Dosage and Administration (2.3) ].

Asthma and Other Pulmonary Disease
The use of OBREDON in patients with acute or severe bronchial asthma in an unmonitored setting or in the absence of resuscitative equipment is contraindicated [ see Contraindications (4) ].

Opioid analgesics and antitussives, including hydrocodone, one of the active ingredients in OBREDON, should not be used in patients with acute febrile illness associated with productive cough or in patients with chronic respiratory disease where interference with ability to clear the tracheobronchial tree of secretions would have a deleterious effect on the patient’s respiratory function.

OBREDON-treated patients with significant chronic obstructive pulmonary disease or cor pulmonale, and those with a substantially decreased respiratory reserve, hypoxia, hypercapnia, or pre-existing respiratory depression are at increased risk of decreased respiratory drive including apnea, even at recommended dosages of OBREDON [ see Warnings and Precautions (5.2) ].

Elderly, Cachectic, or Debilitated Patients:Life-threatening respiratory depression is more likely to occur in elderly, cachectic, or debilitated patients because they may have altered pharmacokinetics or altered clearance compared to younger, healthier patients [ see Warnings and Precautions (5.2) ].

Because of the risk of respiratory depression, avoid the use of opioid antitussives, including OBREDON in patients with compromised respiratory function, patients at risk of respiratory failure, and in elderly, cachectic, or debilitated patients. If OBREDON is prescribed, monitor such patients closely, particularly when initiating OBREDON and when OBREDON is given concomitantlywith other drugs that depress respiration [ see Warnings and Precautions (5.8) ].

5.5 Risk of Accidental Overdose and Death due to Medication Errors

Dosing errors can result in accidental overdose and death. To reduce the risk of overdose and respiratory depression, ensure that the dose of OBREDON is communicated clearly and dispensed accurately [ see Dosage and Administration (2.1) ].

Advise patients to always use an accurate milliliter measuring device when measuring and administering OBREDON. Inform patients that household teaspoon is not an accurate measuring device and such use could lead to overdosage and serious adverse reactions [ see Overdosage (10) ]. For prescriptions where a measuring device is not provided, a pharmacist can provide an appropriate calibrated measuring device and can provide instructions for measuring the correct dose.

5.6 Activities Requiring Mental Alertness: Risks of Driving and Operating Machinery

Hydrocodone, one of the active ingredients in OBREDON, may produce marked drowsiness and impair the mental and/or physical abilities required for the performance of potentially hazardous tasks such as driving a car or operating machinery. Advise patients to avoid engaging in hazardous tasks requiring mental alertness and motor coordination after ingestion of OBREDON. Avoid concurrent use of OBREDON with alcohol or other central nervous system depressants because additional impairment of central nervous system performance may occur [ see Warnings and Precautions (5.8) ].

5.7 Risks from Concomitant Use or Discontinuation of Cytochrome P450 3A4 Inhibitors and Inducers

Concomitant use of OBREDON with a CYP3A4 inhibitor, such as macrolide antibiotics (e.g., erythromycin), azole-antifungal agents (e.g., ketoconazole), and protease inhibitors (e.g., ritonavir), may increase plasma concentrations of hydrocodone and prolong opioid adverse reactions, which may cause potentially fatal respiratory depression [ see Warnings and Precautions (5.2) ], particularly when an inhibitor is added after a stable dose of OBREDON is achieved. Similarly, discontinuation of a CYP3A4 inducer, such as rifampin, carbamazepine, and phenytoin, in OBREDON-treated patients may increase hydrocodone plasma concentrations and prolong opioid adverse reactions.

Concomitant use of OBREDON with CYP3A4 inducers or discontinuation of an CYP3A4 inhibitor could decrease hydrocodone plasma concentrations, decrease opioid efficacy or, possibly, lead to a withdrawal syndrome in a patient who had developed physical dependence to hydrocodone.

Avoid the use of OBREDON in patients who are taking a CYP3A4 inhibitor or inducer. If concomitant use of OBREDON with a CYP3A4 inhibitor or inducer is necessary, monitor patients for signs and symptoms that may reflect opioid toxicity and opioid withdrawal [ see Drug Interactions (7.2, 7.3) ].

5.8 Risks from Concomitant Use with Benzodiazepines or other CNS Depressants

Concomitant use of opioids, including OBREDON, with benzodiazepines, or other CNS depressants, including alcohol, may result in profound sedation, respiratory depression, coma, and death. Because of these risks, avoid use of opioid cough medications in patients taking benzodiazepines, other CNS depressants, or alcohol [ see Drug Interactions (7.1, 7.4) ].

Observational studies have demonstrated that concomitant use of opioid analgesics and benzodiazepines increases the risk of drug-related mortality compared to use of opioids alone. Because of similar pharmacologic properties, it is reasonable to expect similar risk with concomitant use of opioid cough medications and benzodiazepines, other CNS depressants, or alcohol.

Advise both patients and caregivers about the risks of respiratory depression and sedation if OBREDON is used with benzodiazepines, alcohol, or other CNS depressants [ see Patient Counseling Information (17) ].

Patients must not consume alcoholic beverages, or prescription or non-prescription products containing alcohol, while on OBREDON therapy. The co-ingestion of alcohol with OBREDON may result in increased plasma levels and a potentially fatal overdose of hydrocodone [ see Drug Interactions (7.1) ].

5.9 Risks of Use in Patients with Gastrointestinal Conditions

OBREDON is contraindicated in patients with known or suspected gastrointestinal obstruction, including paralytic ileus [ see Contraindications (4) ]. The use of hydrocodone in OBREDON may obscure the diagnosis or clinical course of patients with acute abdominal conditions.

The concurrent use of anticholinergics with OBREDON may produce paralytic ileus [ see Drug Interactions (7.9) ].

The hydrocodone in OBREDON may result in constipation or obstructive bowel disease, especially in patients with underlying intestinal motility disorders. Use with caution in patients with underlying intestinal motility disorders.

The hydrocodone in OBREDON may cause spasm of the sphincter of Oddi, resulting in an increase in biliary tract pressure. Opioids may cause increases in serum amylase [ see Warnings and Precautions (5.15) ]. Monitor patients with biliary tract disease, including acute pancreatitis for worsening symptoms.

5.10 Risks of Use in Patients with Head Injury, Impaired Consciousness, Increased Intracranial Pressure, or Brain Tumors

Avoid the use of OBREDON in patients with head injury, intracranial lesions, or a pre-existing increase in intracranial pressure. In patients who may be susceptible to the intracranial effects of CO2retention (e.g., those with evidence of increased intracranial pressure or brain tumors), OBREDON may reduce respiratory drive, and the resultant CO2retention can further increase intracranial pressure. Furthermore, opioids produce adverse reactions that may obscure the clinical course of patients with head injuries.

5.11 Increased Risk of Seizures in Patients with Seizure Disorders

The hydrocodone in OBREDON may increase the frequency of seizures in patients with seizure disorders, and may increase the risk of seizures occurring in other clinical settings associated with seizures. Monitor patients with a history of seizure disorders for worsened seizure control during OBREDON therapy.

5.12 Severe Hypotension

OBREDON may cause severe hypotension including orthostatic hypotension and syncope in ambulatory patients. There is increased risk in patients whose ability to maintain blood pressure has already been compromised by a reduced blood volume or concurrent administration of certain CNS depressant drugs (e.g., phenothiazines or general anesthetics) [ see Drug Interactions (7.4) ]. Monitor these patients for signs of hypotension after initiating OBREDON.

In patients with circulatory shock, OBREDON may cause vasodilation that can further reduce cardiac output and blood pressure. Avoid the use of OBREDON in patients with circulatory shock.

5.13 Neonatal Opioid Withdrawal Syndrome

OBREDON is not recommended for use in pregnant women. Prolonged use of OBREDON during pregnancy can result in withdrawal in the neonate. Neonatal opioid withdrawal syndrome, unlike opioid withdrawal syndrome in adults, may be life-threatening if not recognized and treated, and requires management according to protocols developed by neonatology experts. Observe newborns for signs of neonatal opioid withdrawal syndrome and manage accordingly. Advise pregnant women using opioids for a prolonged period of the risk of neonatal opioid withdrawal syndrome and ensure that appropriate treatment will be available. [ see Use in Specific Populations (8.1), Patient Counseling Information (17) ]

5.14 Adrenal Insufficiency

Cases of adrenal insufficiency have been reported with opioid use, more often following greater than one month of use. Presentation of adrenal insufficiency may include non-specific symptoms and signs including nausea, vomiting, anorexia, fatigue, weakness, dizziness, and low blood pressure. If adrenal insufficiency is suspected, confirm the diagnosis with diagnostic testing as soon as possible. If adrenal insufficiency is diagnosed, treat with physiologic replacement doses of corticosteroids. Wean the patient off of the opioid to allow adrenal function to recover and continue corticosteroid treatment until adrenal function recovers. Other opioids may be tried as some cases reported use of a different opioid without recurrence of adrenal insufficiency. The information available does not identify any particular opioids as being more likely to be associated with adrenal insufficiency.

5.15 Drug/Laboratory Test Interactions

Because opioid agonists may increase biliary tract pressure, with resultant increase in plasma amylase or lipase levels, determination of these enzyme levels may be unreliable for 24 hours after administration of a dose of OBREDON.

6 ADVERSE REACTIONS

The following serious adverse reactions are described, or described in greater detail, in other sections:

- Addiction, abuse, and misuse [ see Warnings and Precautions (5.1), Drug Abuse and Dependence (9.3) ]
- Life-threatening respiratory depression [ see Warnings and Precautions (5.2, 5.3, 5.4, 5.8), Overdosage (10) ]
- Accidental overdose and death due to medication errors [ see Warnings and Precautions (5.5) ]
- Decreased mental alertness with impaired mental and/or physical abilities [ see Warnings and Precautions (5.6) ]
- Interactions with benzodiazepines and other CNS depressants [ see Warnings and Precautions (5.8), Drug Interactions (7.1, 7.4) ]
- Paralytic ileus, gastrointestinal adverse reactions [ see Warnings and Precautions (5.9) ]
- Increased intracranial pressure [ see Warnings and Precautions (5.10) ]
- Obscured clinical course in patients with head injuries [ see Warnings and Precautions (5.10) ]
- Seizures [ see Warnings and Precautions (5.11) ]
- Severe hypotension [ see Warnings and Precautions (5.12) ]
- Neonatal Opioid Withdrawal Syndrome [ see Warnings and Precautions (5.13) ]
- Adrenal insufficiency [ see Warnings and Precautions (5.14) ]

The following adverse reactions have been identified during clinical studies, in the literature, or during post-approval use of hydrocodone and/or guaifenesin. Because these reactions may be reported voluntarily from a population of uncertain size, it is not always possible to reliably estimate their frequency or establish a causal relationship to drug exposure.

The most common adverse reactions to OBREDON include: Sedation (somnolence, mental clouding, lethargy), impaired mental and physical performance, lightheadedness, dizziness, headache, dry mouth, nausea, vomiting, and constipation.

Other reactions include:

Anaphylaxis:Anaphylaxis has been reported with hydrocodone, one of the ingredients in OBREDON.

Body as a whole:Coma, death, fatigue, falling injuries, lethargy.

Cardiovascular:Peripheral edema, increased blood pressure, decreased blood pressure, tachycardia, chest pain, palpitation, syncope, orthostatic hypotension, prolonged QT interval, hot flush.

Central Nervous System:Facial dyskinesia, insomnia, migraine, increased intracranial pressure, seizure, tremor.

Dermatologic:Flushing, hyperhidrosis, pruritus, rash.

Endocrine/Metabolic:Cases of serotonin syndrome, a potentially life-threatening condition, have been reported during concomitant use of opioids with serotonergic drugs. Cases of adrenal insufficiency have been reported with opioid use, more often following greater than one month of use. Cases of androgen deficiency have occurred with chronic use of opioids.

Gastrointestinal:Abdominal pain, bowel obstruction, decreased appetite, diarrhea, difficulty swallowing, GERD, indigestion, pancreatitis, paralytic ileus, biliary tract spasm (spasm of the sphincter of Oddi).

Genitourinary:Urinary tract infection, ureteral spasm, spasm of vesicle sphincters, urinary retention.

Laboratory:Increases in serum amylase.

Musculoskeletal:Arthralgia, backache, muscle spasm.

Ophthalmic:Miosis (constricted pupils), visual disturbances.

Psychiatric:Agitation, anxiety, confusion, fear, dysphoria, depression.

Reproductive:Hypogonadism, infertility.

Respiratory:Bronchitis, cough, dyspnea, nasal congestion, nasopharyngitis, respiratory depression, sinusitis, upper respiratory tract infection.

Other:Drug abuse, drug dependence, opioid withdrawal syndrome.

Hypoglycemia:Cases of hypoglycemia have been reported in patients taking opioids. Most reports were in patients with at least one predisposing risk factor (e.g., diabetes).

7 DRUG INTERACTIONS

No specific interaction studies have been conducted with OBREDON.

7.1 Alcohol

Concomitant use of alcohol with OBREDON can result in an increase of hydrocodone plasma levels and potentially fatal overdose of hydrocodone. Instruct patients not to consume alcoholic beverages or use prescription or nonprescription products containing alcohol while on OBREDON therapy [ see Warnings and Precautions (5.8), Clinical Pharmacology (12.3) ].

7.2 Inhibitors of CYP3A4 and CYP2D6

The concomitant use of OBREDON and CYP3A4 inhibitors, such as macrolide antibiotics (e.g., erythromycin), azole-antifungal agents (e.g. ketoconazole), or protease inhibitors (e.g., ritonavir), can increase the plasma concentration of hydrocodone, resulting in increased or prolonged opioid effects. These effects could be more pronounced with concomitant use of OBREDON and CYP2D6 and CYP3A4 inhibitors, particularly when an inhibitor is added after a stable dose of OBREDON is achieved [ see Warnings and Precautions (5.7) ]. After stopping a CYP3A4 inhibitor, as the effects of the inhibitor decline, the hydrocodone plasma concentration will decrease [ see Clinical Pharmacology (12.3) ], resulting in decreased opioid efficacy or a withdrawal syndrome in patients who had developed physical dependence to hydrocodone.

Avoid the use of OBREDON while taking a CYP3A4 or CYP2D6 inhibitor. If concomitant use is necessary, monitor patients for respiratory depression and sedation at frequent intervals.

7.3 CYP3A4 Inducers

The concomitant use of OBREDON and CYP3A4 inducers such as rifampin, carbamazepine, or phenytoin, can decrease the plasma concentration of hydrocodone [ see Clinical Pharmacology (12.3) ], resulting in decreased efficacy or onset of a withdrawal syndrome in patients who have developed physical dependence to hydrocodone [ see Warnings and Precautions (5.7) ]. After stopping a CYP3A4 inducer, as the effects of the inducer decline, the hydrocodone plasma concentration will increase [ see Clinical Pharmacology (12.3) ], which could increase or prolong both the therapeutic effects and adverse reactions, and may cause serious respiratory depression.

Avoid the use of OBREDON in patients who are taking CYP3A4 inducers. If concomitant use of a CYP3A4 inducer is necessary, follow the patient for reduced efficacy.

7.4 Benzodiazepines, and Other CNS Depressants

Due to additive pharmacologic effect, the concomitant use of benzodiazepines or other CNS depressants, including alcohol, other sedatives/hypnotics, anxiolytics, tranquilizers, muscle relaxants, general anesthetics, antipsychotics, and other opioids, can increase the risk of hypotension, respiratory depression, profound sedation, coma, and death. Avoid the use of OBREDON in patients who are taking benzodiazepines or other CNS depressants [ see Warnings and Precautions (5.8) ], and instruct patients to avoid consumption of alcohol while on OBREDON [ see Drug Interactions (7.1), Patient Counseling Information (17) ].

7.5 Serotonergic Drugs

The concomitant use of opioids with other drugs that affect the serotonergic neurotransmitter system has resulted in serotonin syndrome. If concomitant use is warranted, carefully observe the patient, particularly during treatment initiation. Discontinue OBREDON if serotonin syndrome is suspected.

7.6 Monoamine Oxidase Inhibitors (MAOIs)

Avoid the use of OBREDON in patients who are taking monoamine oxidase inhibitors (MAOIs) or have taken MAOIs within 14 days. The use of MAOIs or tricyclic antidepressants with hydrocodone, one of the active ingredients in OBREDON, may increase the effect of either the antidepressant or hydrocodone. MAOI interactions with opioids may manifest as serotonin syndrome or opioid toxicity (e.g., respiratory depression, coma).

7.7 Muscle Relaxants

Hydrocodone may enhance the neuromuscular blocking action of skeletal muscle relaxants and produce an increased degree of respiratory depression. Avoid the use of OBREDON in patients taking muscle relaxants. If concomitant use is necessary, monitor patients for signs of respiratory depression that may be greater than otherwise expected.

7.8 Diuretics

Opioids can reduce the efficacy of diuretics by inducing the release of antidiuretic hormone. Monitor patients for signs of diminished diuresis and/or effects on blood pressure and increase the dosage of the diuretic as needed.

7.9 Anticholinergic Drugs

The concomitant use of anticholinergic drugs with OBREDON may increase risk of urinary retention and/or severe constipation, which may lead to paralytic ileus [ see Warnings and Precautions (5.9) ]. Monitor patients for signs of urinary retention or reduced gastric motility when OBREDON is used concomitantly with anticholinergic drugs.

8 USE IN SPECIFIC POPULATIONS

8.1 Pregnancy

Risk Summary

OBREDON is not recommended for use in pregnant women, including during or immediately prior to labor.

Prolonged use of opioids during pregnancy may cause neonatal opioid withdrawal syndrome [ see Warnings and Precautions (5.13), Clinical Considerations ].

There are no available data with OBREDON use in pregnant women to inform a drug-associated risk for adverse developmental outcomes. Published studies with hydrocodone have reported inconsistent findings and have important methodological limitations (see Data).

Reproductive toxicity studies have not been conducted with OBREDON; however, studies are available with individual active ingredients or related active ingredients (see Data).

In animal reproduction studies, hydrocodone administered by the subcutaneous route to pregnant hamsters during the period of organogenesis produced a teratogenic effect at a dose approximately 45 times the maximum recommended human dose (MRHD) (see Data).

Guaifenesin administered by the oral route to pregnant rats during the period of organogenesis was embryolethal at a dose approximately 1 times the MRHD and produced teratogenic effects at a dose approximately 2 times the MRHD (see Data).

Based on the animal data, advise pregnant women of the potential risk to a fetus.

The estimated background risk of major birth defects and miscarriage for the indicated population is unknown. All pregnancies have a background risk of birth defect, loss, or other adverse outcomes. In the U.S. general population, the estimated background risk of major birth defects and miscarriage in clinically recognized pregnancies is 2 to 4% and 15 to 20%, respectively.

Clinical Considerations

Fetal/Neonatal Adverse Reactions
Prolonged use of opioid analgesics during pregnancy for medical or nonmedical purposes can result in physical dependence in the neonate and neonatal opioid withdrawal syndrome shortly after birth.

Neonatal opioid withdrawal syndrome presents as irritability, hyperactivity and abnormal sleep pattern, high pitched cry, tremor, vomiting, diarrhea and failure to gain weight. The onset, duration, and severity of neonatal opioid withdrawal syndrome vary based on the specific opioid used, duration of use, timing and amount of last maternal use, and rate of elimination of the drug by the newborn. Observe newborns for symptoms of neonatal opioid withdrawal syndrome and manage accordingly [ see Warnings and Precautions (5.13) ].

Labor or Delivery
Opioids cross the placenta and may produce respiratory depression and psycho-physiologic effects in neonates. An opioid antagonist, such as naloxone, must be available for reversal of opioid-induced respiratory depression in the neonate. Opioids, including OBREDON, can prolong labor through actions which temporarily reduce the strength, duration, and frequency of uterine contractions. However, this effect is not consistent and may be offset by an increased rate of cervical dilation, which tends to shorten labor. Monitor neonates exposed to opioids during labor for signs of excess sedation and respiratory depression.

Data

Human Data

HydrocodoneA limited number of pregnancies have been reported in published observational studies and postmarketing reports describing hydrocodone use during pregnancy. However, these data cannot definitely establish or exclude any drug-associated risk during pregnancy. Methodological limitations of these observational studies include small sample size and lack of details regarding dose, duration and timing of exposure.

Animal Data

Reproductive toxicity studies have not been conducted with OBREDON; however, studies are available with individual active ingredients or related active ingredients.

HydrocodoneIn an embryofetal development study in pregnant hamsters dosed on gestation day 8 during the period of organogenesis, hydrocodone induced cranioschisis, a malformation, at approximately 45 times the MRHD (on a mg/m^2basis with a maternal subcutaneous dose of 102 mg/kg). Reproductive toxicology studies were also conducted with codeine, an opiate related to hydrocodone. In an embryofetal development study in pregnant rats dosed throughout the period of organogenesis, codeine increased resorptions and decreased fetal weights at a dose approximately 65 times the MRHD of hydrocodone (on a mg/m^2basis with a maternal oral dose of codeine at 120 mg/kg/day); however, these effects occurred in the presence of maternal toxicity. In embryofetal development studies with pregnant rabbits and mice dosed throughout the period of organogenesis, codeine produced no adverse developmental effects at doses approximately 30 and 160 times, respectively, the MRHD of hydrocodone (on a mg/m^2basis with maternal oral doses of codeine at 30 mg/kg/day in rabbits and 600 mg/kg/day in mice).

Guaifenesin
In an embryofetal development study in pregnant rats dosed throughout the period of organogenesis, guaifenesin resulted in fetal death at doses approximately 1 times the MRHD (on a mg/m^2basis with maternal oral doses of 350 mg/kg/day and higher). Guaifenesin also induced hemorrhagic spots and decreases in fetal weight and lengths of full body, skull, fore- and hind-limbs, and tail at doses 1 times the MRHD (on a mg/m^2basis with maternal oral doses of 250 mg/kg/day and higher). Limb and tail defects, increased intercostal space, and improper development of limbs were observed at doses 2 times the MRHD (on a mg/m^2basis with maternal oral doses of 500 mg/kg/day and higher).

8.2 Lactation

Risk Summary

Because of the potential for serious adverse reactions, including excess sedation, respiratory depression, and death in a breastfed infant, advise patients that breastfeeding is not recommended during treatment with OBREDON.

There are no data on the presence of OBREDON in human milk, the effects of OBREDON on the breastfed infant, or the effects of OBREDON on milk production; however, data are available with hydrocodone.

Hydrocodone
Hydrocodone is present in breast milk. Published cases report variable concentrations of hydrocodone and hydromorphone (an active metabolite) in breast milk with administration of immediate-release hydrocodone to nursing mothers in the early post-partum period with relative infant doses of hydrocodone ranging between 1.4 and 3.7%. There are case reports of excessive sedation and respiratory depression in breastfed infants exposed to hydrocodone. No information is available on the effects of hydrocodone on milk production.

Guaifenesin
No information is available on the levels of guaifenesin in breast milk or on milk production.

Clinical Considerations

Infants exposed to OBREDON through breast milk should be monitored for excess sedation and respiratory depression. Withdrawal symptoms can occur in breastfed infants when maternal administration of an opioid is stopped, or when breastfeeding is stopped.

8.3 Females and Males of Reproductive Potential

Infertility
Chronic use of opioids, such as hydrocodone, a component of OBREDON, may cause reduced fertility in females and males of reproductive potential. It is not known whether these effects on fertility are reversible [ see Adverse Reactions (6), Clinical Pharmacology (12.2) ].

8.4 Pediatric Use

OBREDON is not indicated for use in patients younger than 18 years of age because the benefits of symptomatic treatment of cough associated with allergies or the common cold do not outweigh the risks for use of hydrocodone in these patients [ see Indications (1), Warnings and Precautions (5.3) ].

Life-threatening respiratory depression and death have occurred in children who received hydrocodone [ see Warnings and Precautions (5.2) ]. Because of the risk of life-threatening respiratory depression and death, OBREDON is contraindicated in children less than 6 years of age [ see Contraindications (4) ].

8.5 Geriatric Use

Clinical studies have not been conducted with OBREDON in geriatric populations.

Use caution when considering the use of OBREDON in patients 65 years of age or older. Elderly patients may have increased sensitivity to hydrocodone; greater frequency of decreased hepatic, renal, or cardiac function; or concomitant disease or other drug therapy [ see Warnings and Precautions (5.4) ].

Respiratory depression is the chief risk for elderly patients treated with opioids, including OBREDON. Respiratory depression has occurred after large initial doses of opioids were administered to patients who were not opioid-tolerant or when opioids were co-administered with other agents that depress respiration [ see Warnings and Precautions (5.4, 5.8) ].

Hydrocodone is known to be substantially excreted by the kidney, and the risk of adverse reactions to this drug may be greater in patients with impaired renal function. Because elderly patients are more likely to have decreased renal function, monitor these patients closely for respiratory depression, sedation, and hypotension.

8.6 Renal Impairment

The pharmacokinetics of OBREDON has not been characterized in patients with renal impairment. Patients with renal impairment may have higher plasma concentrations than those with normal function [ see Clinical Pharmacology (12.3) ]. OBREDON should be used with caution in patients with severe impairment of renal function, and patients should be monitored closely for respiratory depression, sedation, and hypotension.

8.7 Hepatic Impairment

The pharmacokinetics of OBREDON has not been characterized in patients with hepatic impairment. Patients with severe hepatic impairment may have higher plasma concentrations than those with normal hepatic function [ see Clinical Pharmacology (12.3) ]. Therefore, OBREDON should be used with caution in patients with severe impairment of hepatic function, and patients should be monitored closely for respiratory depression, sedation, and hypotension.

9 DRUG ABUSE AND DEPENDENCE

9.1 Controlled Substance

OBREDON contains hydrocodone, a Schedule II controlled substance.

9.2 Abuse

Hydrocodone
OBREDON contains hydrocodone, a substance with a high potential for abuse similar to other opioids including morphine and codeine. OBREDON can be abused and is subject to misuse, addiction, and criminal diversion [ see Warnings and Precautions (5.1) ].

All patients treated with opioids require careful monitoring for signs of abuse and addiction, since use of opioid analgesic and antitussive products carries the risk of addiction even under appropriate medical use.

Prescription drug abuse is the intentional non-therapeutic use of a prescription drug, even once, for its rewarding psychological or physiological effects.

Drug addiction is a cluster of behavioral, cognitive, and physiological phenomena that develop after repeated substance use and includes: a strong desire to take the drug, difficulties in controlling its use, persisting in its use despite harmful consequences, a higher priority given to drug use than to other activities and obligations, increased tolerance, and sometimes a physical withdrawal.

“Drug-seeking” behavior is very common in persons with substance use disorders. Drug-seeking tactics include emergency calls or visits near the end of office hours, refusal to undergo appropriate examination, testing, or referral, repeated “loss” of prescriptions, tampering with prescriptions, and reluctance to provide prior medical records or contact information for other treating health care provider(s). “Doctor shopping” (visiting multiple prescribers to obtain additional prescriptions) is common among drug abusers and people suffering from untreated addiction. Preoccupation with achieving adequate pain relief can be appropriate behavior in a patient with poor pain control.

Abuse and addiction are separate and distinct from physical dependence and tolerance. Health care providers should be aware that addiction may not be accompanied by concurrent tolerance and symptoms of physical dependence in all addicts. In addition, abuse of opioids can occur in the absence of true addiction.

OBREDON, like other opioids, can be diverted for non-medical use into illicit channels of distribution. Careful record-keeping of prescribing information, including quantity, frequency, and renewal requests, as required by state and federal law, is strongly advised.

Proper assessment of the patient, proper prescribing practices, periodic re-evaluation of therapy, and proper dispensing and storage are appropriate measures that help to limit abuse of opioid drugs.

Guaifenesin
Abuse of guaifenesin has been linked to the formation of kidney stones composed of the major metabolite β-(2-methoxyphenoxy) lactic acid.

Risks Specific to Abuse of OBREDON
OBREDON is for oral use only. Abuse of OBREDON poses a risk of overdose and death. The risk is increased with concurrent use of OBREDON with alcohol and other central nervous system depressants [ see Warnings and Precautions (5.8), Drug Interactions (7.1, 7.4) ].

Parenteral drug abuse is commonly associated with transmission of infectious diseases such as hepatitis and HIV.

9.3 Dependence

Psychological dependence, physical dependence, and tolerance may develop upon repeated administration of opioids; therefore, OBREDON should be prescribed and administered for the shortest duration that is consistent with individual patient treatment goals and patients should be reevaluated prior to refills [ see Dosage and Administration (2.3), Warnings and Precautions (5.1) ].

Physical dependence, the condition in which continued administration of the drug is required to prevent the appearance of a withdrawal syndrome, assumes clinically significant proportions only after several weeks of continued oral opioid use, although some mild degree of physical dependence may develop after a few days of opioid therapy.

If OBREDON is abruptly discontinued in a physically-dependent patient, a withdrawal syndrome may occur. Withdrawal also may be precipitated through the administration of drugs with opioid antagonist activity (e.g., naloxone, nalmefene), mixed agonist/antagonist analgesics (e.g., pentazocine, butorphanol, nalbuphine), or partial agonists (e.g., buprenorphine). Some or all of the following can characterize this syndrome: restlessness, lacrimation, rhinorrhea, yawning, perspiration, chills, myalgia, and mydriasis. Other signs and symptoms also may develop, including irritability, anxiety, backache, joint pain, weakness, abdominal cramps, insomnia, nausea, anorexia, vomiting, diarrhea, or increased blood pressure, respiratory rate, or heart rate.

Infants born to mothers physically dependent on opioids will also be physically dependent and may exhibit respiratory difficulties and withdrawal signs [ see Use in Specific Populations (8.1) ].

10 OVERDOSAGE

Clinical Presentation

Hydrocodone
Acute overdose with hydrocodone is characterized by respiratory depression (a decrease in respiratory rate and/or tidal volume, Cheyne-Stokes respiration, cyanosis), extreme somnolence progressing to stupor or coma, skeletal muscle flaccidity, cold and clammy skin, constricted pupils, and, in some cases, pulmonary edema, bradycardia, partial or complete airway obstruction, atypical snoring, hypotension, hypoglycemia, circulatory collapse, cardiac arrest, and death.

Hydrocodone may cause miosis, even in total darkness. Pinpoint pupils are a sign of opioid overdose but are not pathognomonic (e.g., pontine lesions of hemorrhagic or ischemic origin may produce similar findings). Marked mydriasis rather than miosis may be seen with hypoxia in overdose situations [ see Clinical Pharmacology (12.2) ].

Guaifenesin
Overdosage with guaifenesin can cause depression of the central nervous system. While present in polypharmacy overdoses, one case of overdose with only significant levels of guaifenesin has been reported. Symptoms included slurred speech, shallow respirations, reduced heart rate with rhythm sinus bradycardia, followed by asystole.

Treatment of Overdose
Treatment of overdosage is driven by the overall clinical presentation, and consists of discontinuation of OBREDON together with institution of appropriate therapy. Give primary attention to the reestablishment of adequate respiratory exchange through provision of a patent and protected airway and the institution of assisted or controlled ventilation. Employ other supportive measures (including oxygen and vasopressors) in the management of circulatory shock and pulmonary edema as indicated. Cardiac arrest or arrhythmias will require advanced life-support techniques. Gastric emptying may be useful in removing unabsorbed drug.

The opioid antagonists, naloxone and nalmefene, are specific antidotes for respiratory depression resulting from opioid overdose. For clinically significant respiratory or circulatory depression secondary to hydrocodone overdose, administer an opioid antagonist. An antagonist should not be administered in the absence of clinically significant respiratory depression. Because the duration of opioid reversal is expected to be less than the duration of action of hydrocodone in OBREDON, carefully monitor the patient until spontaneous respiration is reliably reestablished. If the response to an opioid antagonist is suboptimal or only brief in nature, administer additional antagonist as directed by the product’s prescribing information.

Hemodialysis is not routinely used to enhance the elimination of hydrocodone from the body.

11 DESCRIPTION

OBREDON (hydrocodone bitartrate and guaifenesin) oral solution contains hydrocodone, an opioid agonist; and guaifenesin, an expectorant.

Each 5 mL of OBREDON contains 2.5 mg of hydrocodone bitartrate and 200 mg of guaifenesin for oral administration.

OBREDON also contains the following inactive ingredients: artificial raspberry flavor, citric acid, glycerin, methylparaben, potassium citrate, potassium sorbate, propylene glycol, propylparaben, purified water, and saccharin sodium.

Hydrocodone Bitartrate
The chemical name for hydrocodone bitartrate is morphinan-6-one, 4,5-epoxy-3-methoxy-17-methyl-, (5α)-, [R-(R*,R*)]-2,3-dihydroxybutanedioate (1:1), hydrate (2:5). It is also known as 4,5α-Epoxy-3-methoxy-17-methylmorphinan-6-one tartrate (1:1) hydrate (2:5). It occurs as a fine white crystal or crystalline powder, which is derived from the opium alkaloid, thebaine. It has the following structural formula:

C18H21NO3• C4H6O6• 2½H2O MW= 494.50

Guaifenesin
The chemical name for guaifenesin is 3-(2-methoxyphenoxy)-1,2- propanediol. It occurs as a white powder and has the following structural formula:

C10H14O4MW= 198.22

12 CLINICAL PHARMACOLOGY

12.1 Mechanism of Action

Hydrocodone
Hydrocodone is an opioid agonist with relative selectivity for the mu-opioid receptor, although it can interact with other opioid receptors at higher doses. The precise mechanism of action of hydrocodone and other opiates is not known; however, hydrocodone is believed to act centrally on the cough center. In excessive doses, hydrocodone will depress respiration.

Guaifenesin
Guaifenesin is an expectorant, the action of which promotes or facilitates the removal of secretions from the respiratory tract. The precise mechanism of action of guaifenesin is not known; however, it is thought to act as an expectorant by increasing the volume and reducing the viscosity of secretions in the trachea and bronchi. In turn, this may increase the efficiency of the cough reflex and facilitate removal of the secretions.

12.2 Pharmacodynamics

Hydrocodone

Effects on the Central Nervous System
Hydrocodone produces respiratory depression by direct action on brain stem respiratory centers. The respiratory depression involves a reduction in the responsiveness of the brain stem respiratory centers to both increases in carbon dioxide tension and to electrical stimulation.

Hydrocodone causes miosis, even in total darkness. Pinpoint pupils are a sign of opioid overdose but are not pathognomonic (e.g., pontine lesions of hemorrhagic or ischemic origins may produce similar findings). Marked mydriasis rather than miosis may be seen due to hypoxia in overdose situations.

Effects on the Gastrointestinal Tract and Other Smooth Muscle
Hydrocodone causes a reduction in motility associated with an increase in smooth muscle tone in the antrum of the stomach and duodenum. Digestion of food in the small intestine is delayed and propulsive contractions are decreased. Propulsive peristaltic waves in the colon are decreased, while tone may be increased to the point of spasm resulting in constipation. Other opioid-induced effects may include a reduction in biliary and pancreatic secretions, spasm of sphincter of Oddi, and transient elevations in serum amylase.

Effects on the Cardiovascular System
Hydrocodone produces peripheral vasodilation which may result in orthostatic hypotension or syncope. Manifestations of histamine release and/or peripheral vasodilation may include pruritus, flushing, red eyes and sweating and/or orthostatic hypotension.

Effects on the Endocrine System
Opioids inhibit the secretion of adrenocorticotropic hormone (ACTH), cortisol, and luteinizing hormone (LH) in humans [ see Adverse Reactions (6) ]. They also stimulate prolactin, growth hormone (GH) secretion, and pancreatic secretion of insulin and glucagon.
Chronic use of opioids may influence the hypothalamic-pituitary-gonadal axis, leading to androgen deficiency that may manifest as low libido, impotence, erectile dysfunction, amenorrhea, or infertility. The causal role of opioids in the clinical syndrome of hypogonadism is unknown because the various medical, physical, lifestyle, and psychological stressors that may influence gonadal hormone levels have not been adequately controlled for in studies conducted to date [ see Adverse Reactions (6) ].

Effects on the Immune System
Opioids have been shown to have a variety of effects on components of the immune system in in vitro and animal models. The clinical significance of these findings is unknown. Overall, the effects of opioids appear to be modestly immunosuppressive.

Concentration–Adverse Reaction Relationships
There is a relationship between increasing hydrocodone plasma concentration and increasing frequency of dose-related opioid adverse reactions such as nausea, vomiting, CNS effects, and respiratory depression. In opioid-tolerant patients, the situation may be altered by the development of tolerance to opioid-related adverse reactions.

12.3 Pharmacokinetics

Absorption
Following a single 10 mL oral dose of OBREDON, the geometric mean Cmaxand AUC0-inffor hydrocodone were 12.6 ng/ml and 80.9 ng·hr/ml, respectively, and the geometric mean Cmaxand AUC0-inffor guaifenesin were 3.7 mcg/ml and 4.2 mcg·hr/ml, respectively. The median time to maximum concentration in plasma for hydrocodone and guaifenesin was about 1.25 hours and 20 minutes, respectively. Food has no significant effect on the extent of absorption of hydrocodone, while the effect of food on guaifenesin systemic exposure is not considered to be clinically meaningful.

Distribution
Although the extent of protein binding of hydrocodone in human plasma has not been definitively determined, structural similarities to related opioid analgesics suggest that hydrocodone is not extensively protein bound. As most agents in the 5-ring morphinan group of semi-synthetic opioids bind plasma protein to a similar degree (range 19% [hydromorphone] to 45% [oxycodone]), hydrocodone is expected to fall within this range.

Elimination

Metabolism
Hydrocodone exhibits a complex pattern of metabolism, including N-demethylation, O-demethylation, and 6keto reduction to the corresponding 6-α-and 6-β-hydroxy metabolites. CYP3A4 mediated N-demethylation to norhydrocodone is the primary metabolic pathway of hydrocodone with a lower contribution from CYP2D6 mediated O-demethylation to hydromorphone. Hydromorphone is formed from the O-demethylation of hydrocodone and may contribute to the total analgesic effect of hydrocodone. Therefore, the formation of these and related metabolites can, in theory, be affected by other drugs [ see Drug Interactions (7) ]. Published in vitro studies have shown that N-demethylation of hydrocodone to form norhydrocodone can be attributed to CYP3A4 while O-demethylation of hydrocodone to hydromorphone is predominantly catalyzed by CYP2D6 and to a lesser extent by an unknown low affinity CYP enzyme.

Excretion
Hydrocodone and its metabolites are eliminated primarily in the kidneys. The mean plasma half-life of hydrocodone is approximately 5 hours.

The mean plasma half-life of guaifenesin is approximately 1 hour.

13 NONCLINICAL TOXICOLOGY

13.1 Carcinogenesis, Mutagenesis, Impairment of Fertility

Carcinogenicity, mutagenicity, and fertility studies have not been conducted with OBREDON; however, published information is available for the individual active ingredients or related active ingredients.

Hydrocodone
Carcinogenicity studies were conducted with codeine, an opiate related to hydrocodone. Two-year studies in F344/N rats and B6C3F1 mice were conducted to assess the carcinogenic potential of codeine. No evidence of tumorigenicity was observed in male and female rats at codeine dietary doses up to 70 and 80 mg/kg/day (approximately equivalent to 40 and 45 times the MRHD of hydrocodone on a mg/m^2basis, respectively). No evidence of tumorigenicity was observed in male and female mice at codeine dietary doses up to 400 mg/kg/day (approximately equivalent to 110 times the MRHD of hydrocodone on a mg/m^2basis).

Mutagenicity studies with hydrocodone have not been conducted.

Fertility studies with hydrocodone have not been conducted.

Guaifenesin
Carcinogenicity, mutagenicity, and fertility studies with guaifenesin have not been conducted

16 HOW SUPPLIED/STORAGE AND HANDLING

OBREDON (hydrocodone bitartrate and guaifenesin) 2.5 mg/200 mg per 5mL is a clear, raspberry flavored oral solution supplied as:
White HDPE bottles of 4 fl oz (118 mL): NDC 58716-433-04
White HDPE bottles of 16 fl oz (473 mL): NDC 58716-433-16

Store solution at 20° to 25°C (68° to 77°F). [See USP Controlled Room Temperature.]

Dispense in a tight, light-resistant container, as defined in the USP, with a child-resistant closure.

Ensure that patients have an oral dosing dispenser that measures the appropriate volume in milliliters. Counsel patients on how to utilize an oral dosing dispenser and correctly measure the oral suspension as prescribed.

17 PATIENT COUNSELING INFORMATION

Advise the patient to read the FDA-approved patient labeling (Medication Guide).

Addiction, Abuse, and Misuse
Inform patients that the use of OBREDON, even when taken as recommended, can result in addiction, abuse, and misuse, which can lead to overdose and death [ see Warnings and Precautions (5.1) ]. Instruct patients not to share OBREDON with others and to take steps to protect OBREDON Oral Solution from theft or misuse.

Important Dosing and Administration Instructions
Instruct patients how to measure and take the correct dose of OBREDON. Advise patients to measure OBREDON with an accurate milliliter measuring device. Patients should be informed that a household teaspoon is not an accurate measuring device and could lead to overdosage. Advise patients to ask their pharmacist to recommend an appropriate measuring device and for instructions for measuring the correct dose [ see Dosage and Administration (2.1), Warnings and Precautions (5.5) ]. Advise patients not to increase the dose or dosing frequency of OBREDON because serious adverse events such as respiratory depression may occur with overdosage [ see Warnings and Precautions (5.2), Overdosage (10) ].

Life-Threatening Respiratory Depression
Inform patients of the risk of life-threatening respiratory depression, including information that the risk is greatest when starting OBREDON and that it can occur even at recommended dosages [ see Warnings and Precautions (5.2)] . Advise patients how to recognize respiratory depression and to seek medical attention if breathing difficulties develop.

Accidental Ingestion
Inform patients that accidental ingestion, especially by children, may result in respiratory depression or death [ see Warnings and Precautions (5.2) ]. Instruct patients to take steps to store OBREDON securely and to properly dispose of unused OBREDON in accordance with the local state guidelines and/or regulations.

Activities Requiring Mental Alertness
Advise patients to avoid engaging in hazardous tasks that require mental alertness and motor coordination such as operating machinery or driving a motor vehicle as OBREDON may produce marked drowsiness [ see Warnings and Precautions (5.6) ].

Interactions with Benzodiazepines and Other Central Nervous System Depressants, Including Alcohol
Inform patients and caregivers that potentially fatal additive effects may occur if OBREDON is used with benzodiazepines or other CNS depressants, including alcohol. Advise patients to avoid concomitant use of OBREDON with benzodiazepines or other CNS depressants and instruct patients not to consume alcoholic beverages, as well as prescription and over-the-counter products that contain alcohol, during treatment with OBREDON [ see Warnings and Precautions (5.8), Drug Interactions (7.1, 7.4) ].

Constipation
Advise patients of the potential for severe constipation [ see Warnings and Precautions (5.9), Adverse Reactions (6) ].

Anaphylaxis
Inform patients that anaphylaxis has been reported with ingredients contained in OBREDON. Advise patients how to recognize such a reaction and when to seek medical attention [ see Contraindications (4), Adverse Reactions (6) ].

MAOI Interaction
Inform patients not to take OBREDON while using or within 14 days of stopping any drugs that inhibit monoamine oxidase. Patients should not start MAOIs while taking OBREDON [ see Drug Interactions (7.6) ].

Hypotension
Inform patients that OBREDON may cause orthostatic hypotension and syncope. Instruct patients how to recognize symptoms of low blood pressure and how to reduce the risk of serious consequences should hypotension occur (e.g., sit or lie down, carefully rise from a sitting or lying position) [ see Warnings and Precautions (5.12) ].

Pregnancy
Advise patients that use of OBREDON is not recommended during pregnancy [ see Use in Specific Populations (8.1) ].

Neonatal Opioid Withdrawal Syndrome
Inform female patients of reproductive potential that use of OBREDON during pregnancy can result in neonatal opioid withdrawal syndrome, which may be life-threatening if not recognized and treated [ see Warnings and Precautions (5.13), Use in Specific Populations (8.1) ].

Embryo-Fetal Toxicity
Inform female patients of reproductive potential that OBREDON can cause fetal harm and to inform their healthcare provider of a known or suspected pregnancy [ see Use in Specific Populations (8.1) ].

Lactation
Advise women that breastfeeding is not recommended during treatment with OBREDON [ see Use in Specific Populations (8.2) ].

Infertility
Inform patients that chronic use of opioids, such as hydrocodone, a component of OBREDON, may cause reduced fertility. It is not known whether these effects on fertility are reversible [ see Use in Specific Populations (8.3) ].

Adrenal Insufficiency
Inform patients that OBREDON could cause adrenal insufficiency, a potentially life-threatening condition. Adrenal insufficiency may present with non-specific symptoms and signs such as nausea, vomiting, anorexia, fatigue, weakness, dizziness, and low blood pressure. Advise patients to seek medical attention if they experience a constellation of these symptoms [ see Warnings and Precautions (5.14) ].

Serotonin Syndrome
Inform patients that OBREDON could cause a rare but potentially life-threatening condition resulting from concomitant administration of serotonergic drugs. Warn patients of the symptoms of serotonin syndrome and to seek medical attention right away if symptoms develop. Instruct patients to inform their physicians if they are taking, or plan to take serotonergic medications. [ see Adverse Reactions (6), Drug Interactions (7.5) ].

Disposal of Unused OBREDON
Advise patients to properly dispose of unused OBREDON. Advise patients to throw the drug in the household trash following these steps. 1) Remove them from their original containers and mix them with an undesirable substance, such as used coffee grounds or kitty litter (this makes the drug less appealing to children and pets, and unrecognizable to people who may intentionally go through the trash seeking drugs). 2) Place the mixture in a sealable bag, empty can, or other container to prevent the drug from leaking or breaking out of a garbage bag, or to dispose of in accordance with local state guidelines and/or regulations.

Manufactured by:
Sovereign Pharmaceuticals, LLC
Fort Worth, TX 76118

U.S. Patent numbers 9,549,907; 9,808,431; 10,105,324

Medication Guide
OBREDON (Oh-bre-don)
(hydrocodone bitartrate and guaifenesin) oral solution, C-II

What is the most important information I should know about OBREDON?

OBREDON is not for children under 18 years of age.

OBREDON can cause serious side effects, including:

- Addiction, abuse and misuse.Taking OBREDON or other medicines that contain an opioid can cause addiction, abuse and misuse, which can lead to overdose and death. This can happen even if you take OBREDON exactly as prescribed by your healthcare provider. Your risk of addiction, abuse, and misuse is increased if you or a family member has a history of drug or alcohol abuse or addiction, or mental health problems.
  - Do notshare your OBREDON with other people.
  - Keep OBREDON in a safe place away from children.
- Life-threatening breathing problems (respiratory depression).OBREDON can cause breathing problems (respiratory depression) that can happen at any time during treatment and can lead to death. Your risk of breathing problems is greatest when you first start taking OBREDON, are taking other medicines that can cause breathing problems, have certain lung problems, are elderly or have certain other health problems. Children are at higher risk for respiratory depression.Breathing problems can happen even if you take OBREDON exactly as prescribed by your healthcare provider.
  Call your healthcare provider or get emergency medical help right away if anyone taking OBREDON has any of the symptoms below:
  - increased sleepiness
  - confusion
  - difficulty breathing
  - shallow breathing
  - limpness
- Keep OBREDON in a safe place away from children.Accidental use of even 1 dose of OBREDON, especially by a child, is a medical emergency and can cause breathing problems (respiratory depression) which can lead to death. If a child accidentally takes OBREDON, get emergency medical help right away.
- Overdose and death due to medicine dosing errors.Overdose and death can happen if you measure the wrong dose of OBREDON. Always use an accurate milliliter (mL) measuring device to measure the correct amount of OBREDON. Do notuse a household teaspoon to measure your medicine. You may accidentally take too much. You can ask your pharmacist for the measuring device you should use and how to measure the correct dose.
- Breathing problems (respiratory depression) that can lead to death and opioid withdrawalcan happen if you start taking or stop taking other medicines while taking OBREDON, including:
  - certain antibiotics
  - certain medicines to treat a fungal infection
  - certain medicines to treat Human Immunodeficiency Virus (HIV)-1 infection, Acquired Immune Deficiency Syndrome (AIDS), or Hepatitis C
  - rifampin
  - carbamazepine
  - phenytoin
    Tell your healthcare provider if you take any of these medicines. Ask your healthcare provider or pharmacist if you are not sure if your medicine is listed above.
- Severe drowsiness, breathing problems (respiratory depression), coma and deathcan happen in people who take OBREDON with benzodiazepines or other central nervous system depressants, including alcohol.
  - Do nottake benzodiazepines or any medicine that can cause drowsiness or sleepiness during treatment with OBREDON.
  - Do notdrink alcohol or take prescription or over-the-counter medicines that contain alcohol during treatment with OBREDON.
- Opioid withdrawal in a newborn.Use of OBREDON during pregnancy can cause withdrawal symptoms in your newborn baby that could be life-threatening if not recognized and treated. You should not take OBREDON if you are pregnant. Tell your healthcare provider right away if you are pregnant or think you may be pregnant.

What is OBREDON?

- OBREDON is a prescription medicine used in adults to treat a cough and to loosen mucus that you can have with a common cold. OBREDON contains 2 medicines, hydrocodone and guaifenesin. Hydrocodone is an opioid (narcotic) cough suppressant. Guaifenesin is an expectorant.
- OBREDON is a federal controlled substance (C-II) because it contains hydrocodone that can be abused or lead to dependence.Keep OBREDON in a safe place to prevent misuse and abuse. Selling or giving away OBREDON may harm others, and is against the law. Tell your healthcare provider if you have abused or been dependent on alcohol, prescription medicines or street drugs.

Who should not take OBREDON?

OBREDON is not for children under 18 years of age.See “What is the most important information I should know about OBREDON?”

Do not take OBREDON if you:

- have severe breathing problems (respiratory depression) or breathing problems caused by asthma. See “ What is the most important information I should know about OBREDON?”
- have a blockage (obstruction) in your bowel such as a paralytic ileus.
- are allergic to hydrocodone, guaifenesin, or any of the ingredients in OBREDON. See the end of this Medication Guide for a complete list of ingredients.

Ask your healthcare provider if you have any questions about this information.

Before you take OBREDON, tell your healthcare provider about all of your medical conditions, including if you:

- have a drug addiction
- have lung or breathing problems
- have a fever and are coughing up mucus
- have had a recent head injury
- have had a brain tumor or other brain problem
- have or have had seizures
- have pain in your stomach-area (abdomen)
- have constipation or other bowel problems
- have bile duct or pancreas problems
- have prostate problems
- have problems with your urinary tract or difficulty urinating
- have kidney or liver problems
- have adrenal gland problems
- have low blood pressure
- plan to have surgery
- are pregnant or plan to become pregnant. OBREDON can harm your unborn baby. See “What is the most important information I should know about OBREDON?”
- are breastfeeding or plan to breastfeed. Hydrocodone passes into your breast milk and can cause serious side effects in your baby including increased sleepiness, breathing problems (respiratory depression), and death. It is not known if guaifenesin passes into your breast milk. You and your healthcare provider should decide if you will take OBREDON or breastfeed. You should not do both.
- plan to have children. OBREDON may affect the ability to have a child in females and males (fertility problems). It is not known if these fertility problems will be reversible, even after you stop taking OBREDON. Talk to your healthcare provider if this is a concern for you.

Tell your healthcare provider about all the medicines you take,including prescription and over-the-counter medicines, vitamins, and herbal supplements.

Taking OBREDON with certain other medicines can cause side effects or affect how well OBREDON or the other medicines work. Do not start or stop taking other medicines without talking to your healthcare provider.

Especially tell your healthcare provider if you:

- See “What is the most important information I should know about OBREDON?”
- take pain medicines such as opioids (narcotics).
- take cold or allergy medicines that contain antihistamines or cough suppressants.
- drink alcohol.
- take muscle relaxants.
- take certain medicines used to treat mood, anxiety, psychotic or thought disorders, or depression, including monoamine oxidase inhibitors (MAOIs), tricyclics, selective serotonin reuptake inhibitors (SSRIs), selective serotonin-norepinephrine reuptake inhibitors (SNRIs), or antipsychotics.
- take medicines to lower your blood pressure.
- take water pills (diuretics).
- take medicines called “anticholinergics” used to treat certain health problems including asthma, chronic obstructive pulmonary disease (COPD), or stomach problems.

Ask your healthcare provider if you are not sure if you take one of these medicines.

How should I take OBREDON?

- See “What is the most important information I should know about OBREDON?”
- Take OBREDON exactly as your healthcare provider tells you to take it. Do not change your dose without talking to your healthcare provider.
- Take OBREDON by mouth only.
- Take OBREDON using an accurate milliliter (mL) measuring device. If you do not have one, ask your pharmacist to give you a measuring device to help you measure the correct amount of OBREDON. Do not use a household teaspoon to measure your medicine. You may accidently take too much.
- Do notoverfill the measuring device.
- Rinse your measuring device with water after each use.
- If you take too much OBREDON, call your healthcare provider or go to the nearest hospital emergency room right away.
- Tell your healthcare provider if your cough does not get better within 5 days of treatment with OBREDON.

What should I avoid while taking OBREDON?

- Avoid driving a car or operating machinery during treatment with OBREDON. OBREDON can cause you to be drowsy, slow your thinking and motor skills, and may affect your vision.
- Do notdrink alcohol during treatment with OBREDON. Drinking alcohol can increase your chances of having serious side effects.

Avoid the use of OBREDON if you:

- are pregnant. Use of OBREDON during pregnancy can cause withdrawal symptoms in your newborn baby that could be life-threatening if not recognized and treated. Tell your healthcare provider right away if you are pregnant or think you may be pregnant.
- are breastfeeding. Use of OBREDON while breastfeeding can cause severe breathing problems (respiratory depression) in your breastfed infant that could be life-threatening.
- take a medicine called a monoamine oxidase inhibitor (MAOI). Avoid taking an MAOI within 14 days after you stop taking OBREDON. Avoid starting OBREDON if you stopped taking an MAOI in the last 14 days.

What are the possible side effects of OBREDON?

OBREDON can cause serious side effects, including:

- See “What is the most important information I should know about OBREDON?”
- Bowel problems including severe constipation or stomach pain.See “ Who should not take OBREDON?”
- Increased pressure in your head (intracranial).Avoid the use of OBREDON if you have a head injury or have been told that you have changes in the tissue of your brain (brain lesions) or increased pressure in your head.
- Increased risk of seizures in people with seizure disorders.If you have a seizure disorder, OBREDON may increase how often you have a seizure.
- Low blood pressure.A sudden drop in blood pressure can happen in some people during treatment with OBREDON and this may cause you to feel dizzy, faint, lightheaded, or weak, especially when you stand up (orthostatic hypotension). Your risk of having this problem may be increased if you take OBREDON with certain other medicines that lower blood pressure. If you have any of these symptoms while taking OBREDON, sit or lie down. Do not change your body position too fast. Get up slowly from sitting or lying down.
- Adrenal gland problems.OBREDON can cause serious and life-threatening adrenal gland problems. Your healthcare provider may do blood tests to check for adrenal gland problems. Call your healthcare provider right away if you have any of these symptoms:
  - nausea
  - vomiting
  - not wanting to eat (anorexia)
  - fatigue
  - weakness
  - dizziness
  - low blood pressure

The most common side effects of OBREDON include:

- sleepiness
- confusion
- coordination problems
- decrease in mental and physical performance
- lack of energy
- lightheadedness
- dizziness
- headache
- dry mouth
- nausea
- vomiting
- constipation

These are not all the possible side effects of OBREDON.

Call your doctor for medical advice about side effects. You may report side effects to FDA at 1-800-FDA-1088.

How should I store OBREDON?

- Store OBREDON at room temperature between 20°F to 25°F (68°C to 77°C).
- Store OBREDON in a tightly closed container, in a dry, cool place away from heat or direct sunlight.
- Keep OBREDON and all medicines out of the reach of children.

How should I dispose of OBREDON?

Remove unused OBREDON from the container and mix it with an undesirable, non-toxic substance such as cat litter or used coffee grounds to make it less appealing to children and pets. Place the mixture in a container such as a sealed plastic bag and throw it away in the household trash. You can also follow your state or local guidelines on how to safely throw away OBREDON.

General information about the safe and effective use of OBREDON.
Medicines are sometimes prescribed for purposes other than those listed in a Medication Guide. Do not use OBREDON for a condition for which it was not prescribed. Do not give OBREDON to other people, even if they have the same symptoms that you have. It may harm them.
You can ask your pharmacist or healthcare provider for information about OBREDON that is written for health professionals.

What are the ingredients in OBREDON?

Active ingredients:hydrocodone bitartrate and guaifenesin

Inactive ingredients:artificial raspberry flavor, citric acid, glycerin, methylparaben, potassium citrate, potassium sorbate, propylene glycol, propylparaben, purified water, and saccharin sodium.

Manufactured by: Sovereign Pharmaceuticals, LLC, Fort Worth, TX 76118
For more information, call 1-855-461-5102.

This Medication Guide has been approved by the U.S. Food and Drug Administration.

Revised: April 2018

Principal Display Panel-16 fl oz. Bottle

16 fl oz. Bottle Label

NDC -58716-433-16

OBREDON (hydrocodone bitartrate and guaifenesin) oral solution CII
2.5 mg/ 200 mg per 5 mL

Contains:

Hydrocodone Bitartrate ... 2.5 mg/5 mL
WARNING: May be habit forming.

Guaifenesin ..................... 200 mg/5 mL

Rx Only

16 fl oz. (473 mL)

USUAL DOSAGE:See Package Insert for Complete Dosage Recommendations.
Dispense in a tight, light-resistant container with a child-resistant closure.

WARNING: KEEP THIS AND ALL MEDICATIONS OUT OF THE REACH OF CHILDREN.

Store at 20° to 25°C (68° to 77°F). [See USP Controlled Room Temperature]

Tamper evident by foil seal under cap. Do not use if foil seal is broken or missing.

Manufactured by:
Sovereign Pharmaceuticals, LLC
06/2018